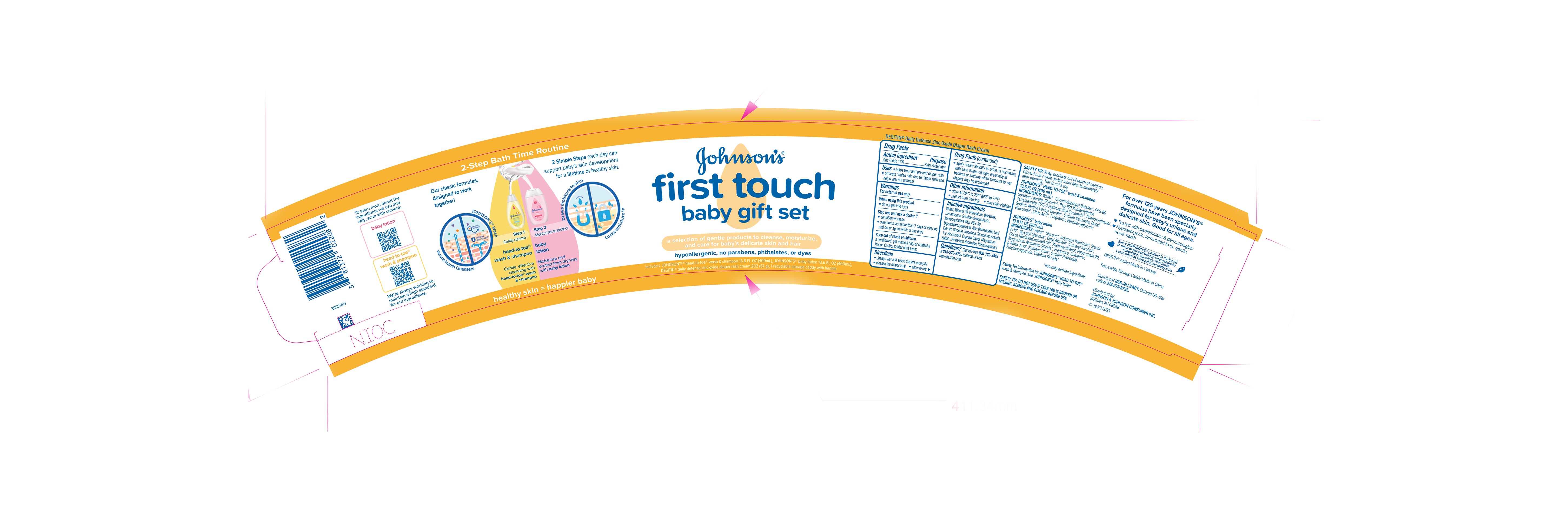 DRUG LABEL: Johnsons First Touch Baby Gift Set
NDC: 69968-0739 | Form: KIT | Route: TOPICAL
Manufacturer: Kenvue Brands LLC
Category: otc | Type: HUMAN OTC DRUG LABEL
Date: 20241125

ACTIVE INGREDIENTS: ZINC OXIDE 130 mg/1 g
INACTIVE INGREDIENTS: SORBITAN SESQUIOLEATE; GLYCERIN; ALPHA-TOCOPHEROL ACETATE; 1,2-HEXANEDIOL; CAPRYLYL GLYCOL; MAGNESIUM SULFATE, UNSPECIFIED; POTASSIUM HYDROXIDE; PHENOXYETHANOL; MINERAL OIL; YELLOW WAX; MICROCRYSTALLINE WAX; WATER; PETROLATUM; DIMETHICONE; PEG-30 DIPOLYHYDROXYSTEARATE; ALOE VERA LEAF; TROPOLONE

Johnson’s® first touch baby gift set Desitin® Daily Defense Zinc Oxide Diaper Rash Cream

Drug Facts

Active ingredient

Zinc Oxide 13%

Purpose

Skin Protectant

Uses

- helps treat and prevent diaper rash
- protects chafed skin due to diaper rash and helps seal out wetness

Warnings

For external use only

When using this product

- do not get into eyes

Stop use and ask a doctor if

- condition worsens
- symptoms last more than 7 days or clear up and occur again within a few days

Keep out of reach of children. If swallowed, get medical help or contact a Poison Control Center right away.

Directions

- change wet and soiled diapers promptly
- cleanse the diaper area
- allow to dry
- apply cream liberally as often as necessary, with each diaper change, especially at bedtime or anytime when exposure to wet diapers may be prolonged

Other information

- store at 20°C to 25°C (68°F to 77°F)
- protect from freezing
- may stain clothing

Inactive ingredients

Water, Mineral Oil, Petrolatum, Beeswax, Dimethicone, Sorbitan Sesquioleate, Microcrystalline Wax, PEG-30 Dipolyhydroxystearate, Aloe Barbadensis Leaf Extract, Glycerin, Tropolone, Tocopheryl Acetate, 1,2-Hexanediol, Caprylyl Glycol, Magnesium Sulfate, Potassium Hydroxide, Phenoxyethanol.

Questions?

Call toll-free 800-720-3843 or 215-273-8755 (collect) or visit www.desitin.com

Distributed by:
JOHNSON & JOHNSON
CONSUMER INC.
Skillman, NJ 08558

PRINCIPAL DISPLAY PANEL - Kit Bag

Johnson’s®

first touch

baby gift set

a selection of gentle products to cleanse, moisturize,

and care for baby’s delicate skin and hair

hypoallergenic, no parabens, phthalates, or dyes

Includes: JOHNSON’S® head-to-toe® wash & shampoo 13.6 FL OZ (400mL), JOHNSON’S® baby lotion 13.6 FL OZ (400mL),

DESITIN® daily defense zinc oxide diaper rash cream 2OZ (57 g), 1 recyclable storage caddy with handle